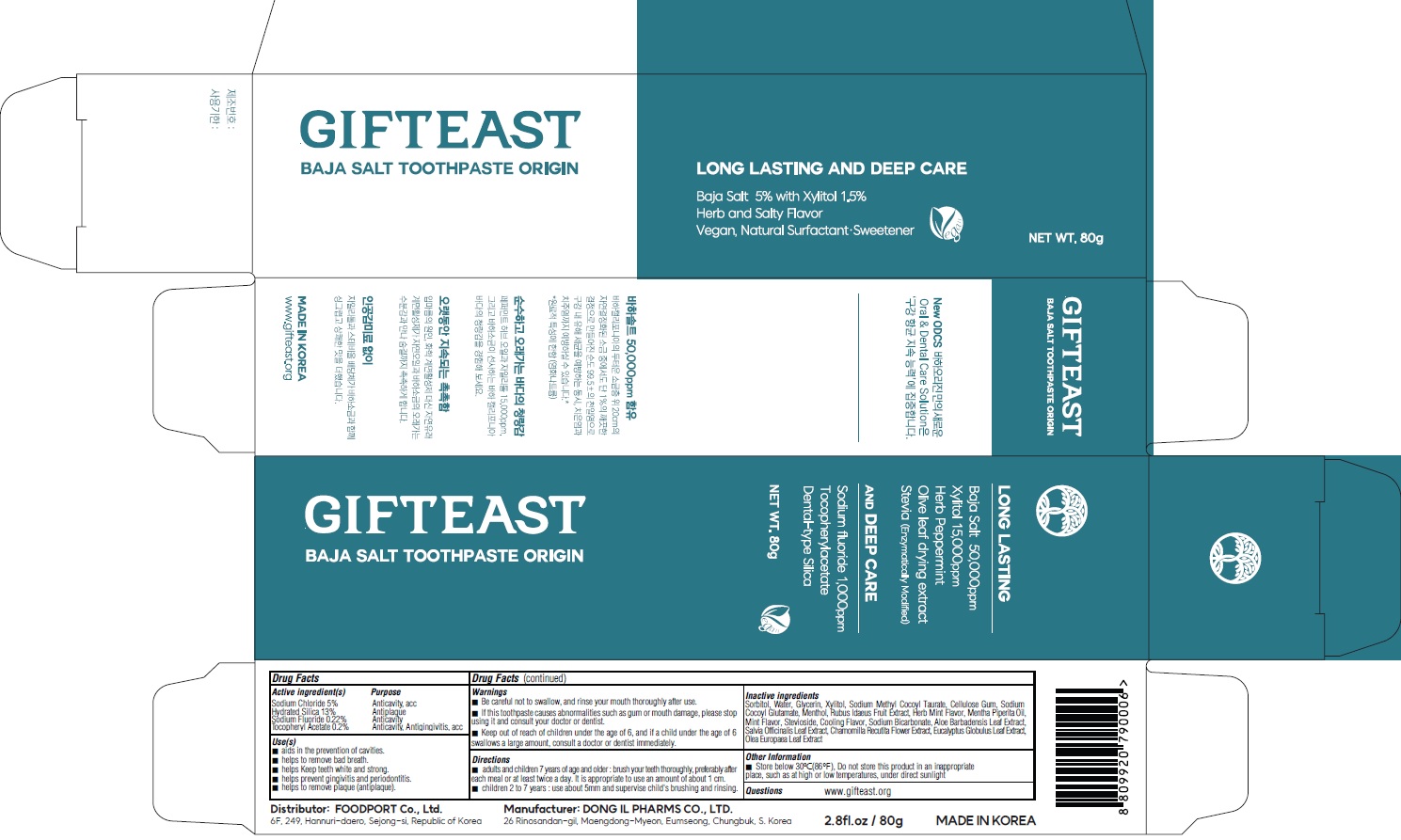 DRUG LABEL: GIFTEAST BAJA SALT TOOTHPASTE ORIGIN
NDC: 83445-020 | Form: PASTE, DENTIFRICE
Manufacturer: FOODPORT
Category: otc | Type: HUMAN OTC DRUG LABEL
Date: 20230517

ACTIVE INGREDIENTS: Sodium Chloride 5.0 g/100 g; HYDRATED SILICA 13.0 g/100 g; Sodium Fluoride 0.22 g/100 g; .ALPHA.-TOCOPHEROL ACETATE 0.2 g/100 g
INACTIVE INGREDIENTS: Sorbitol; Water; Glycerin; Xylitol

Active ingredient(s)

Sodium Chloride 5%
Hydrated Silica 13%
Sodium Fluoride 0.22%
Tocopheryl Acetate 0.2%

Inactive ingredients

Sorbitol, Water, Glycerin, Xylitol, Sodium Methyl Cocoyl Taurate, Cellulose Gum, Sodium Cocoyl Glutamate, Menthol, Rubus Idaeus Fruit Extract, Herb Mint Flavor, Mentha Piperita Oil, Mint Flavor, Stevioside, Cooling Flavor, Sodium Bicarbonate, Aloe Barbadensis Leaf Extract, Salvia Officinalis Leaf Extract, Chamomilla Recutita Flower Extract, Eucalyptus Globulus Leaf Extract, Olea Europaea Leaf Extract

Purpose

Anticavity, acc
Antiplague
Anticavity
Anticavity, Antigingivitis, acc

Warnings

■ Be careful not to swallow, and rinse your mouth thoroughly after use.
■ If this toothpaste causes abnormalities such as gum or mouth damage, please stop using it and consult your doctor or dentist.
■ Keep out of reach of children under the age of 6, and if a child under the age of 6 swallows a large amount, consult a doctor or dentist immediately.

■ Keep out of reach of children under the age of 6, and if a child under the age of 6 swallows a large amount, consult a doctor or dentist immediately.

Use(s)

■ aids in the prevention of cavities.
■ helps to remove bad breath.
■ helps Keep teeth white and strong.
■ helps prevent gingivitis and periodontitis.
■ helps to remove plaque (antiplague).

Directions

■ adults and children 7 years of age and older : brush your teeth thoroughly, preferably after each meal or at least twice a day. It is appropriate to use an amount of about 1 cm.
■ children 2 to 7 years : use about 5mm and supervise child's brushing and rinsing

Other Information

■ Store below 30℃(86℉), Do not store this product in an inappropriate place, such as at high or low temperatures, under direct sunlight

Questions

www.gifteast.org